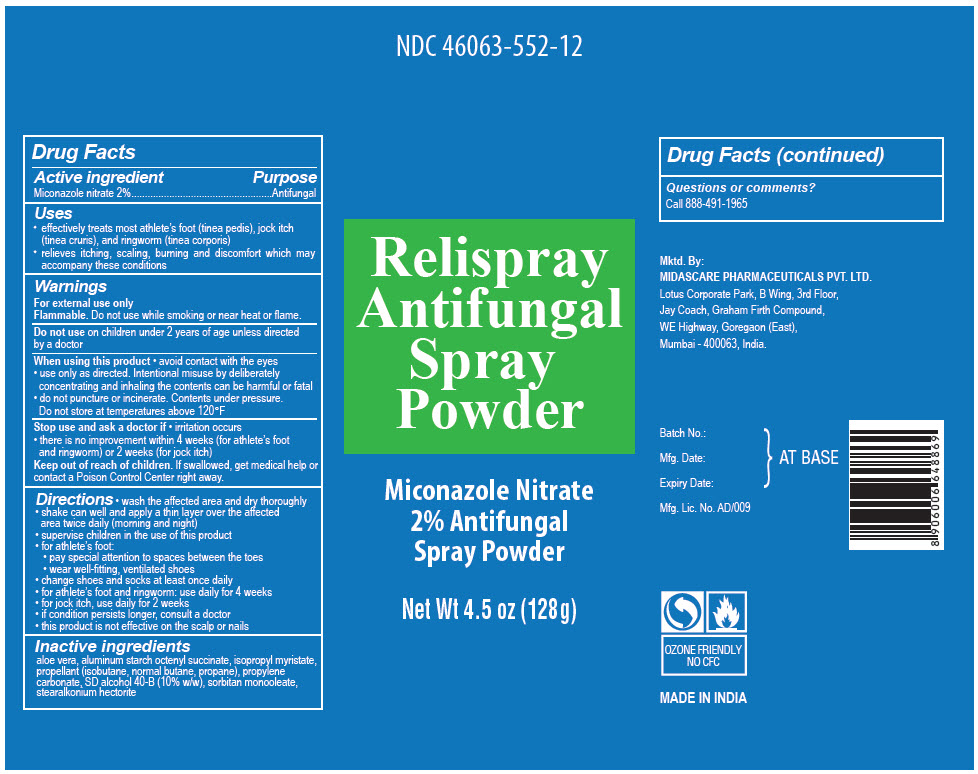 DRUG LABEL: Relispray Antifungal Powder
NDC: 46063-552 | Form: AEROSOL, SPRAY
Manufacturer: Midas-Care Pharmaceuticals Pvt. Ltd.
Category: otc | Type: HUMAN OTC DRUG LABEL
Date: 20241217

ACTIVE INGREDIENTS: Miconazole Nitrate 0.02 g/1 g
INACTIVE INGREDIENTS: ALOE VERA LEAF; ALUMINUM STARCH OCTENYLSUCCINATE; Isopropyl Myristate; LIQUEFIED PETROLEUM GAS; Propylene carbonate; ALCOHOL; Sorbitan monooleate; Stearalkonium hectorite

Relispray Antifungal Spray Powder

Drug Facts

Active ingredient

Miconazole nitrate 2%

Purpose

Antifungal

Uses

- effectively treats most athlete's foot (tinea pedis), jock itch (tinea cruris), and ringworm (tinea corporis)
- relieves itching, scaling, burning and discomfort which may accompany these conditions

Warnings

For external use only

Flammable. Do not use while smoking or near heat or flame.

Do not use on children under 2 years of age unless directed by a doctor

When using this product

- avoid contact with the eyes
- use only as directed. Intentional misuse by deliberately concentrating and inhaling the contents can be harmful or fatal
- do not puncture or incinerate. Contents under pressure.
  Do not store at temperatures above 120°F

Stop use and ask a doctor if

- irritation occurs
- there is no improvement within 4 weeks (for athlete's foot and ringworm) or 2 weeks (for jock itch)

Keep out of reach of children. If swallowed, get medical help or contact a Poison Control Center right away.

Directions

- wash the affected area and dry thoroughly
- shake can well and apply a thin layer over the affected area twice daily (morning and night)
- supervise children in the use of this product
- for athlete's foot:
  - pay special attention to spaces between the toes
  - wear well-fitting, ventilated shoes
- change shoes and socks at least once daily
- for athlete's foot and ringworm: use daily for 4 weeks
- for jock itch, use daily for 2 weeks
- if condition persists longer, consult a doctor
- this product is not effective on the scalp or nails

Inactive ingredients

aloe vera, aluminum starch octenyl succinate, isopropyl myristate, propellant (isobutane, normal butane, propane), propylene carbonate, SD alcohol 40-B (10% w/w), sorbitan monooleate, stearalkonium hectorite

Questions or comments?

Call 888-491-1965

PRINCIPAL DISPLAY PANEL - 128 g Can Label

NDC 46063-552-12

Relispray
Antifungal
Spray
Powder

Miconazole Nitrate
2% Antifungal
Spray Powder

Net Wt 4.5 oz (128g)